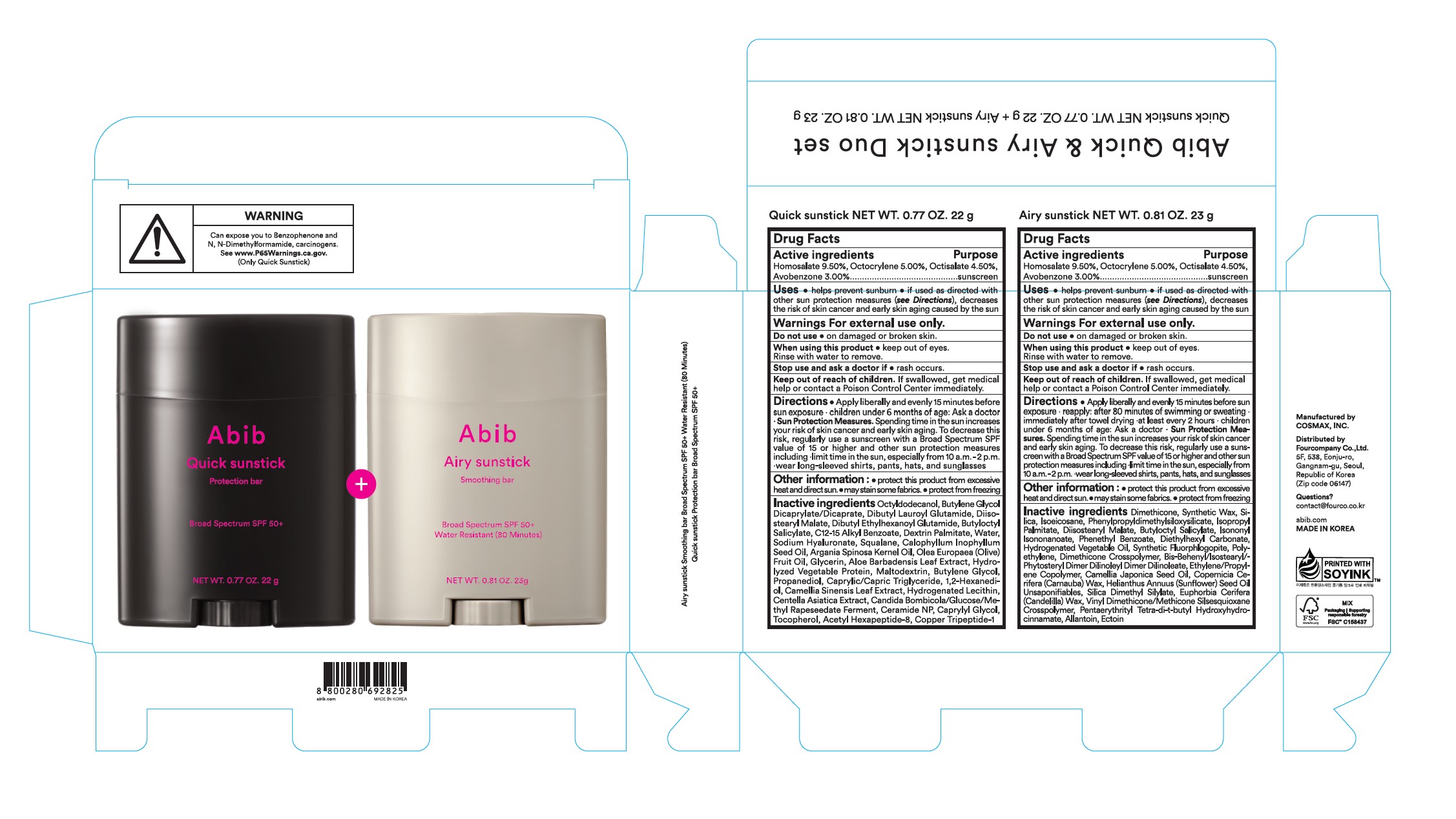 DRUG LABEL: ABIB QUICK AND AIRY SUNSTICK DUO SET
NDC: 73676-316 | Form: KIT | Route: TOPICAL
Manufacturer: FOURCOMPANY CO., LTD.
Category: otc | Type: HUMAN OTC DRUG LABEL
Date: 20250502

ACTIVE INGREDIENTS: HOMOSALATE 9.5 g/100 g; AVOBENZONE 3 g/100 g; OCTOCRYLENE 5 g/100 g; OCTISALATE 4.5 g/100 g; AVOBENZONE 3 g/100 g; OCTOCRYLENE 5 g/100 g; OCTISALATE 4.5 g/100 g; HOMOSALATE 9.5 g/100 g
INACTIVE INGREDIENTS: HYDROGENATED PALM KERNEL OIL; DIETHYLHEXYL CARBONATE; MAGNESIUM POTASSIUM ALUMINOSILICATE FLUORIDE; BUTYLOCTYL SALICYLATE; PPG-15; PHYTOSTERYL/ISOSTEARYL/CETYL/STEARYL/BEHENYL DIMER DILINOLEATE; ISOEICOSANE; ALLANTOIN; SUNFLOWER OIL UNSAPONIFIABLES; ECTOINE; DIMETHICONE; DIMETHICONE CROSSPOLYMER (450000 MPA.S AT 12% IN CYCLOPENTASILOXANE); PHENETHYL BENZOATE; SYNTHETIC WAX (1200 MW); ISONONYL ISONONANOATE; PENTAERYTHRITOL TETRAKIS(3-(3,5-DI-TERT-BUTYL-4-HYDROXYPHENYL)PROPIONATE); CAMELLIA JAPONICA SEED OIL; HIGH DENSITY POLYETHYLENE; CANDELILLA WAX; SILICA DIMETHYL SILYLATE; VINYL DIMETHICONE/METHICONE SILSESQUIOXANE CROSSPOLYMER; SILICON DIOXIDE; POLYMETHYLSILSESQUIOXANE/TRIMETHYLSILOXYSILICATE; DIISOSTEARYL MALATE; ISOPROPYL PALMITATE; CARNAUBA WAX; TOCOPHEROL; CENTELLA ASIATICA; OLIVE OIL; 1,2-HEXANEDIOL; GLYCERIN; ALKYL (C12-15) BENZOATE; ANHYDROUS DEXTROSE; MALTODEXTRIN; BUTYLENE GLYCOL; WATER; BUTYLOCTYL SALICYLATE; DIBUTYL LAUROYL GLUTAMIDE; TAMANU OIL; MEDIUM-CHAIN TRIGLYCERIDES; CERAMIDE NP; DIISOSTEARYL MALATE; ALOE VERA LEAF; METHYL RAPESEEDATE; BUTYLENE GLYCOL DICAPRYLATE/DICAPRATE; DIBUTYL ETHYLHEXANOYL GLUTAMIDE; SQUALANE; HYDROLYZED SENEGALIA MACROSTACHYA SEED PROTEIN (ENZYMATIC; 800 MW); HYALURONATE SODIUM; CAPRYLYL GLYCOL; OCTYLDODECANOL; STARMARELLA BOMBICOLA; PROPANEDIOL; DEXTRIN PALMITATE (CORN; 20000 MW); ARGAN OIL; GREEN TEA LEAF; ACETYL HEXAPEPTIDE-8; HYDROGENATED SOYBEAN LECITHIN; PREZATIDE COPPER

Abib Quick & Airy sunstick Duo set

Active Ingredients

Homosalate 9.50% Octocrylene 5.00% Octisalate 4.50% Avobenzone 3.00%.

Purpose

sunscreen

Uses

- helps prevent sunburn
- if used as directed with other sun protection measures (see Directions), decreases the risk of skin cancer and early skin aging caused by the su

Warnings

For external use only.

Do not use on damaged or broken skin

When using this product keep out of eyes. Rinse with water to remove

Stop use and ask a doctor if rash occurs

Keep out of reach of children. If swallowed, get medical help or contact a Poison Control Center immediately.

Directions

- apply liberally and evenly 15 minutes before sun exposure. children under 6 months of age: ask a doctor. Sun protection measures: spending time in the sun increases your risk of skin cancer and early aging. To decrease this risk, regularly use a sunscreen with a Broad Spectrum SPF value of 15 or higher and other sun protection measures including: limit time in the sun, especially from 10 a.m. - 2 p.m., wear long-sleeved shirts, pants, hats, and sunglasses

Other information

protect this product from excessive heat and direct sun. may stain some fabrics. protect from freezing

Inactives ingredients

Octyldodecanol, Butylene Glycol Dicaprylate/Dicaprate, Dibutyl Lauroyl Glutamide, Diisostearyl Malate, Dibutyl Ethylhexanoyl Glutamide, Butyloctyl Salicylate, C12-15 Alkyl Benzoate, Dextrin Palmitate, Water, Sodium Hyaluronate, Squalane, Calophyllum Inophyllum Seed Oil, Argania Spinosa Kegnel Oil, Olea Euro paea (Olive) Fruit Oil, Glycerin, Aloe Barbadensis Leaf Extract, Hydrolyzed Vegetable Protein, Maltodextrin, Butylene Glycol, Propanediol, Caprylic/Capric Trigly ceride, 1,2-Hexanediol, Camellia Sinensis Leaf Extract, Hydrogenated Lecithin, Centella Asiatica Extract, Candida Bombicola/Glucose/Methyl Rapeseedate Fer ment, Ceramide NP, Caprylyl Glycol, Tocopherol, Acetyl Hexapeptide-8, Copper Tripeptide-1

Active ingredients

Homosalate 9.50%, Octocrylene 5.00%, Octisalate 4.50%, Avobenzone 3.00%

Purpose

sunscreen

Uses

- help prevent sunburn
- if used as directed with other sun protection measures (see Directions), deacreases the risk of skin cancer and early skin aging caused by the sun

Warnings

For external use only.

Do not use on damaged or broken skin

When using this product keep out of eyes. Rinse with water to remove

Stop use and ask a doctor if rash occurs

Keep out of reach of children. If swallowed, get medical help or contact a Poison Control Center immediately.

Directions

apply liberally and evenly 15 minutes before sun exposure. reapply: after 80 minutes of swimming or sweating. immediately after towel drying. at least every 2 hours. children under 6 months of age: ask a doctor. Sun protection measures. spending time in the sun increases your risk of skin cancer and early aging. To decrease this risk, regularly use a sunscreen with a Broad Spectrum SPF value of 15 or higher and other sun protection measures including: limit time in the sun, especially from 10 a.m. - 2 p.m., wear long-sleeved shirts, pants, hats, and sunglasses

Other information

protect this product from excessive heat and direct sun. may stain some fabrics. protect from freezing

Inactive ingredients

Dimethicone, Synthetic Wax, Silica, Isoeicosane, Phenylpropy ldimethylsiloxy silicate, Isopropyl Palmitate, Disostearyl Malate, Butylocty/ Salicylate, Isononyl Isononanoate, Phenethyl Benzoate, Diethylhexyl Carbonate, Hydrogenated Vegetable Oil, Synthetic Fluorphlogopite, Polyethylene, Dimethicone Crosspolymer, Bis-Behenyl/Isostearyl/Phytosteryl Dimer Dilinoleyl Dimer Dilinoleate, Ethylene/Propylene Copolymer, Camellia Japonica Seed Oil,Copernicia Cerifera (Carnauba) Wax, Helianthus Annuus (Sunflower) Seed Oil Unsaponifiables, Silica Dimethyl Silylate, Euphorbia Cerifera (Candelilla) Wax, Vinyl Dimethicone/Methicone Silsesquioxane Crosspolymer, Pentaerythrityl Tetra-di-t-butyl Hydroxyhydrocinnamate, Allantoin, Ectoin

Abib Quick & Airy sunstick Duo set

Quick sunstick NET WT. 0.77 OZ. 22g + Airy sunstick NET WT. 0.81 OZ. 23g